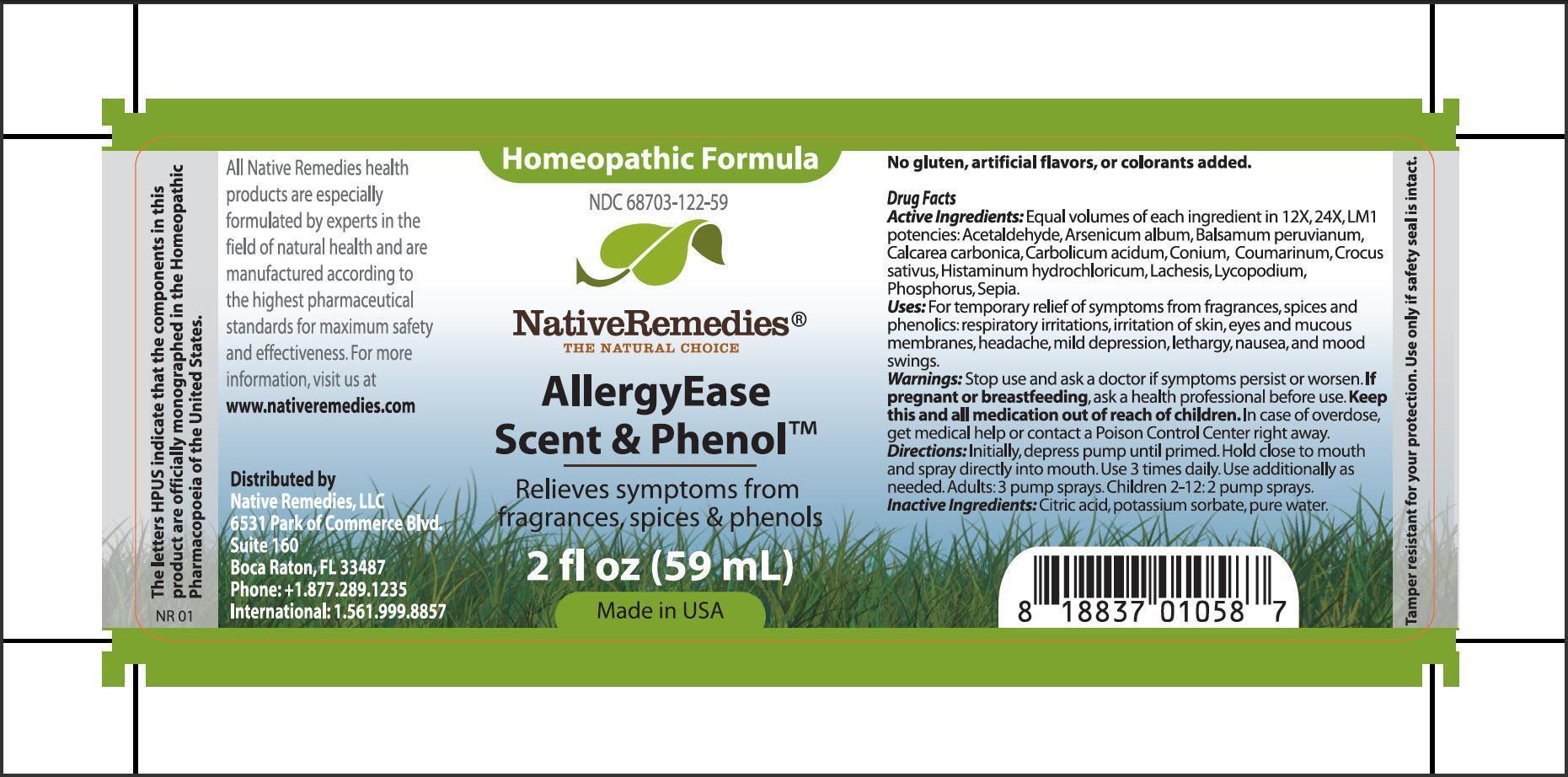 DRUG LABEL: AllergyEase Scent and Phenol
NDC: 68703-122 | Form: SPRAY
Manufacturer: Native Remedies, LLC
Category: homeopathic | Type: HUMAN OTC DRUG LABEL
Date: 20130729

ACTIVE INGREDIENTS: ACETALDEHYDE 12 [hp_X]/59 mL; ARSENIC TRIOXIDE 12 [hp_X]/59 mL; BALSAM PERU 12 [hp_X]/59 mL; OYSTER SHELL CALCIUM CARBONATE, CRUDE 12 [hp_X]/59 mL; PHENOL 12 [hp_X]/59 mL; CONIUM MACULATUM FLOWERING TOP 12 [hp_X]/59 mL; COUMARIN 12 [hp_X]/59 mL; SAFFRON  12 [hp_X]/59 mL; HISTAMINE DIHYDROCHLORIDE 12 [hp_X]/59 mL; LACHESIS MUTA VENOM 12 [hp_X]/59 mL; LYCOPODIUM CLAVATUM SPORE 12 [hp_X]/59 mL; PHOSPHORUS 12 [hp_X]/59 mL; SEPIA OFFICINALIS JUICE 12 [hp_X]/59 mL
INACTIVE INGREDIENTS: CITRIC ACID MONOHYDRATE; POTASSIUM SORBATE; WATER

AllergyEase Scent and Phenol

PURPOSE

Relieves symptoms from fragrances, spices and phenols

Drug Facts
Active Ingredients:Equal volumes of each ingredient in 12X, 24X, LM1 potencies: Acetaldehyde, Arsenicum album, Balsamum peruvianum, Calcarea carbonica, Carbolicum acidum, Conium, Coumarinum, Crocus sativus, Histaminum hydrochloricum, Lachesis, Lycopodium, Phosphorus, Sepia

INDICATIONS AND USAGE

Uses:For temporary relief of symptoms from fragrances, spices and phenolics: respiratory irritations, irritation of skin, eyes and mucous membranes, headache, mild depression, lethargy, nausea, and mood swing

WARNINGS

Warnings: Stop use and ask a doctor if symptoms persist or worsen

PREGNANCY OR BREAST FEEDING

If pregnant or breastfeeding, ask a health professional before use

KEEP OUT OF REACH OF CHILDREN

Keep this and all medication out of reach of children

OVERDOSAGE

In case of overdose, get medical help or contact a Poison Control Center right away

DOSAGE AND ADMINISTRATION

Directions:Initially, depress pump until primed. Hold close to mouth and spray directly into mouth. Use 3 times daily. Use additionally as needed. Adults: 3 pump sprays. Children 2-12: 2 pump sprays

Inactive Ingredients:Citric acid, potassium sorbate, pure water

PATIENT COUNSELING INFORMATION

The letters HPUS indicate that the component in this product are officially monographed in the Homeopathic Pharmacopoeia of the United States.

All Native Remedies health products are especially formulated by expert in the field of natural health and are manufactured according to the highest pharmaceutical standards for maximum safety and effectiveness. For more information visit us at www.nativeremedies.com

Distributed by
Native Remedies, LLC
6531 Park of Commerce Blvd.
Suite 160
Boca Raton, FL 33487
Phone : +1.877.589.1235
International: 1.561.999.8857

No gluten, artificial flavors, or colorants added

STORAGE AND HANDLING

Tamper resistant for your protection. Use only if safety seal is intact.